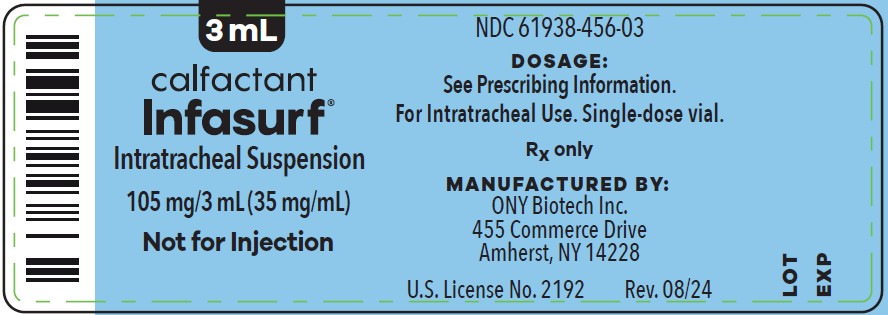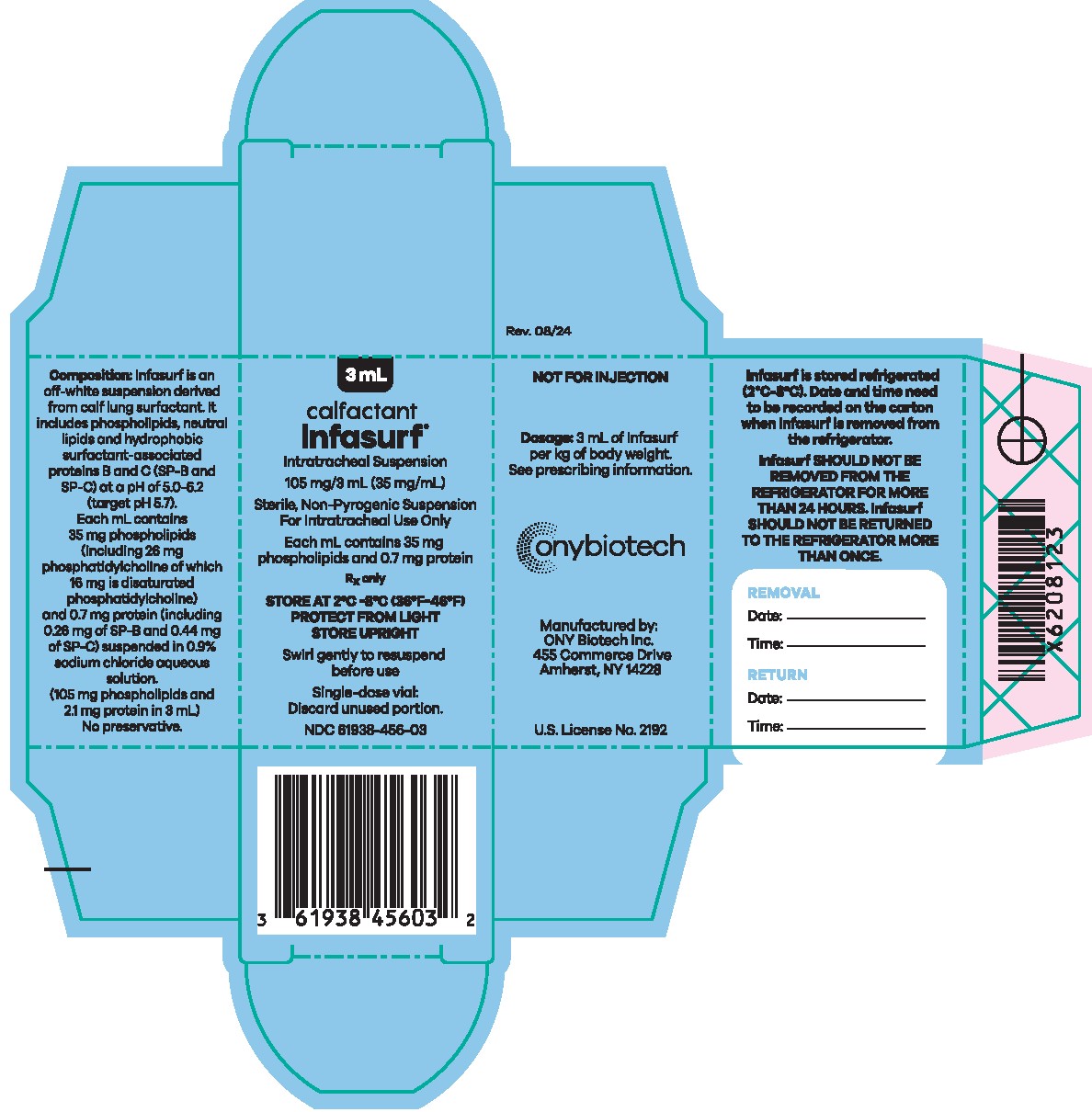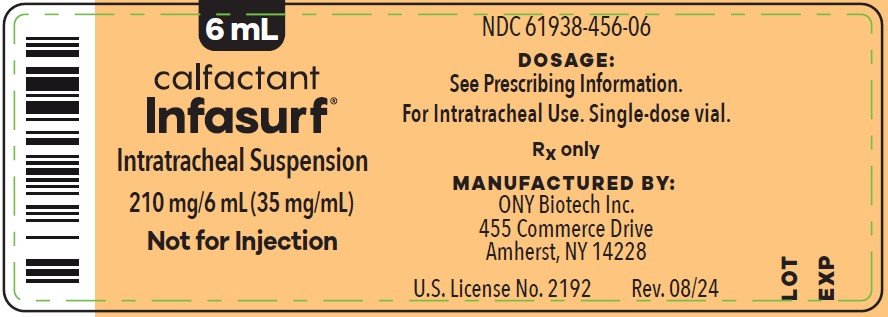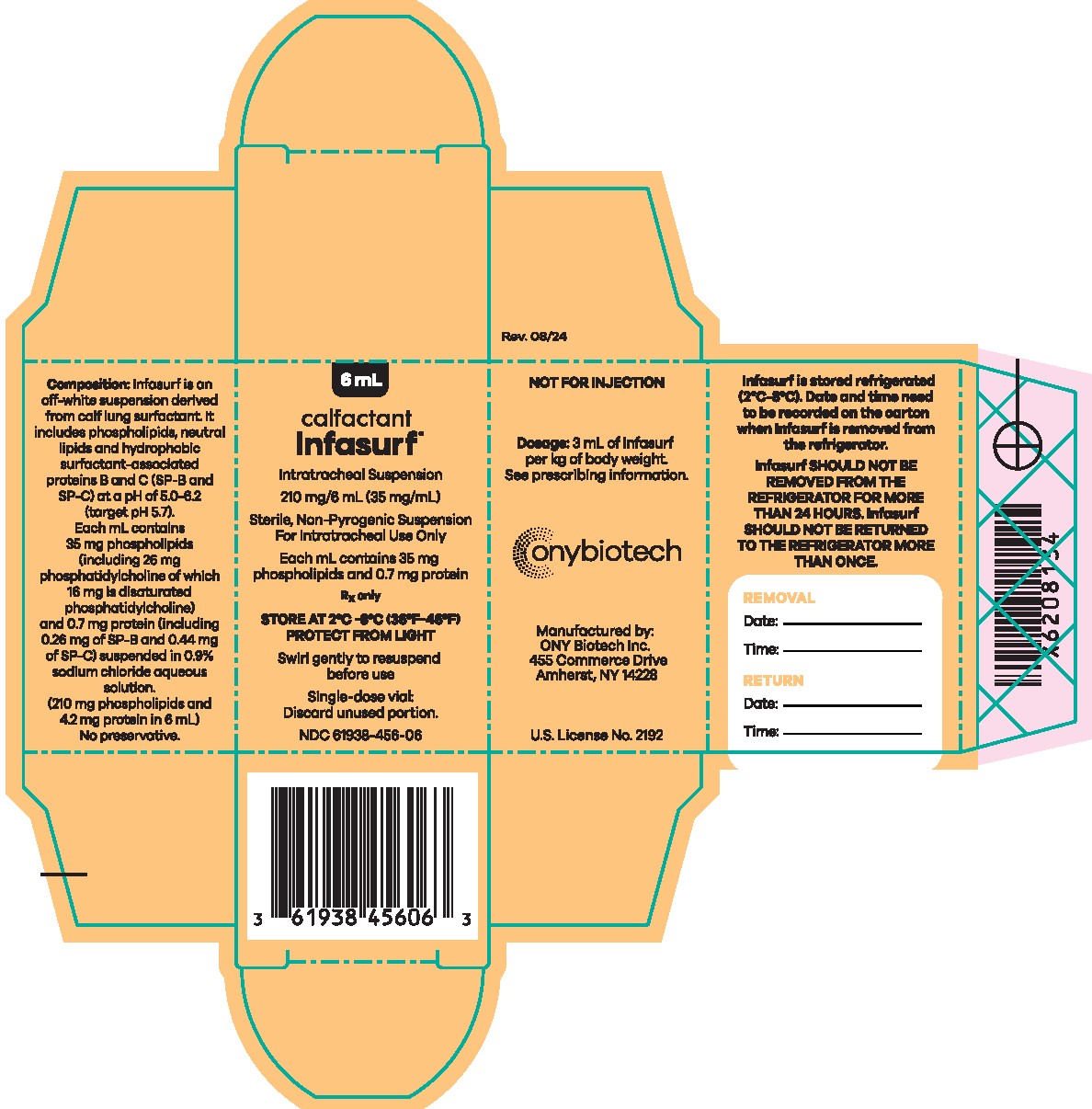 DRUG LABEL: INFASURF
NDC: 61938-456 | Form: SUSPENSION
Manufacturer: ONY Biotech Inc.
Category: prescription | Type: HUMAN PRESCRIPTION DRUG LABEL
Date: 20250107

ACTIVE INGREDIENTS: CALFACTANT 35.7 mg/1 mL
INACTIVE INGREDIENTS: SODIUM CHLORIDE

HIGHLIGHTS OF PRESCRIBING INFORMATION

These highlights do not include all the information needed to use INFASURF®safely and effectively. See full prescribing information for INFASURF.
INFASURF®(calfactant) intratracheal suspension
Initial U.S. Approval: 1998

1 INDICATIONS AND USAGE

INFASURF®is a surfactant indicated:

- to reduce the risk of respiratory distress syndrome (RDS) in preterm neonates < 29 weeks gestational age at risk for RDS. (1)
- for the rescue treatment of preterm neonates ≤72 hours of age with RDS who require endotracheal intubation. (1)

2 DOSAGE AND ADMINISTRATION

- For intratracheal administration only (2)
- The recommended dose of INFASURF is 3 mL/kg body weight at birth. (2.2)
- Up to 3 doses of INFASURF can be administered. (2.2)
- Doses should not be given more frequently than every 12 hours. (2.2)
- Administration instructions: (2.3)
- Side-port adapter into the endotracheal tube: two equal aliquots while ventilation is continued over 20 to 30 breaths for each aliquot.
- 5-French feeding catheter inserted into the endotracheal tube: four equal aliquots with the catheter removed between each of the instillations and mechanical ventilation resumed for 0.5 to 2 minutes.

3 DOSAGE FORMS AND STRENGTHS

Intratracheal Suspension:

- 105 mg/3 mL (35 mg/mL) single-dose vial (3)
- 210 mg/6 mL (35 mg/mL) single-dose vial (3)

4 CONTRAINDICATIONS

None.

5 WARNINGS AND PRECAUTIONS

- Acute Changes in Oxygenation and Lung Compliance: INFASURF administration can rapidly affect oxygenation and lung compliance. Frequently monitor neonates after administration of INFASURF to adjust oxygen therapy and ventilator pressures appropriately. (5.1)
- Administration-Related Adverse Reactions: Adverse reactions associated with INFASURF include cyanosis, bradycardia, airway obstruction, and reflux of INFASURF into the endotracheal tube. In the event of these adverse reactions, stop INFASURF administration, and take appropriate measures to alleviate the adverse reactions and resume INFASURF with appropriate monitoring. (5.2)
- Intraventricular Hemorrhage and Periventricular Leukomalacia: Some INFASURF-treated neonates developed intraventricular hemorrhage and periventricular leukomalacia in randomized clinical trials. (5.3)

6 ADVERSE REACTIONS

Most common adverse reactions associated with the use of INFASURF are cyanosis (65%), airway obstruction (39%), bradycardia (34%), reflux of surfactant into the endotracheal tube (21%), requirement for manual ventilation (16%), and reintubation (3%).

To report SUSPECTED ADVERSE REACTIONS, contact ONY Biotech Inc. at 1-877-663-4179 or FDA at 1-800-FDA-1088 or www.fda.gov/medwatch.

See 17 for PATIENT COUNSELING INFORMATION

FULL PRESCRIBING INFORMATION

1 INDICATIONS AND USAGE

INFASURF is indicated:

- to reduce the risk of respiratory distress syndrome (RDS) in preterm neonates <29 weeks of gestational age at risk for RDS.
- for the rescue treatment of RDS in preterm neonates ≤72 hours of age with RDS who require endotracheal intubation.

2 DOSAGE AND ADMINISTRATION

2.1 Recommended Dosage

The recommended dose of INFASURF is 3 mL/kg body weight at birth administered intratracheally through an endotracheal tube. INFASURF can be administered every 12 hours for a total of up to three doses.

To reduce the risk of RDS in preterm neonates <29 weeks of gestational age at risk for RDS, administer INFASURF within 30 minutes after birth.

2.2 Preparation Instructions

- INFASURF does not require reconstitution. Do not dilute or sonicate.
- INFASURF does not need to reach room temperature before administration.
- Gently swirl or agitate the INFASURF intratracheal suspension vial for redispersion. Do not shake.
- Visually inspect the INFASURF intratracheal suspension for discoloration prior to administration. The color of the INFASURF intratracheal suspension should be off-white. Discard the INFASURF vial if the intratracheal suspension is discolored. Visible flecks in the intratracheal suspension and foaming at the surface are normal.
- Using a 20-gauge or larger needle and syringe to avoid excessive foaming, withdraw INFASURF from the vial.
- Discard unopened INFASURF vials stored at room temperature for more than 24 hours.
- Discard unused INFASURF after the initial vial entry.

2.3 Administration Instructions

INFASURF should be administered by healthcare providers who are experienced in the acute care of neonates with RDS who require intubation. Two attendants should be present to facilitate dosing; one to instill the INFASURF, the other to monitor the neonate.

Administer INFASURF intratracheally through an endotracheal tube using the prepared syringe [ see Dosage and Administration (2.2)] using either of the following two methods. Instill the INFASURF dose through a:

- Side-port adapter into the endotracheal tube as two equal aliquots of 1.5 mL/kg each. During and after each aliquot that is instilled, position the neonate with either the right or the left side dependent and maintain ventilation over 20 to 30 breaths for each aliquot, with small bursts timed only during the inspiratory cycles. Between aliquot administration evaluate the respiratory status and reposition to the other side.

- 5-French feeding catheter inserted into the endotracheal tube as four equal aliquots of 0.75 mL/kg each. During and after each aliquot is instilled, position the neonate in four different positions (i.e., prone, supine, right, and left lateral) to facilitate even distribution of INFASURF. Remove the catheter between each of the instillations and resume mechanical ventilation for 0.5 to 2 minutes.

After INFASURF administration, frequently monitor neonate oxygenation and ventilatory status [ see Warnings and Precautions (5.1)].

3 DOSAGE FORMS AND STRENGTHS

Intratracheal Suspension: INFASURF (calfactant) is an off-white suspension available as:

- 105 mg/3 mL (35 mg/mL) single-dose vial
- 210 mg/6 mL (35 mg/mL) single-dose vial

4 CONTRAINDICATIONS

None.

5 WARNINGS AND PRECAUTIONS

5.1 Acute Changes in Oxygenation and Lung Compliance

The administration of exogenous surfactants, including INFASURF, can rapidly affect oxygenation and lung compliance. Frequently monitor neonates who receive INFASURF so that oxygen and ventilatory support can be modified in response to changes in respiratory status. INFASURF should only be administered by those trained and experienced in the care, resuscitation, and stabilization of preterm neonates with RDS who require intubation.

5.2 Administration-Related Adverse Reactions

Administration-related adverse reactions associated with INFASURF use included cyanosis, bradycardia, airway obstruction, and reflux of INFASURF into the endotracheal tube. These adverse reactions occurred more frequently in neonates who received repeat doses of INFASURF at 12-hour intervals than neonates that received colfosceril palmitate, the comparator, in randomized controlled trials (Trials 1 and 3) [ see Clinical Studies (14)]. If these adverse reactions occur during INFASURF administration, stop INFASURF and institute appropriate measures to alleviate these adverse reactions and resume INFASURF with appropriate monitoring.

5.3 Intraventricular Hemorrhage and Periventricular Leukomalacia

An increased proportion of INFASURF-treated neonates compared to colfosceril palmitate-treated neonates in randomized clinical trials (Trials 1 and 3) [ see Clinical Studies (14)] developed intraventricular hemorrhage and periventricular leukomalacia. These adverse reactions were not associated with increased mortality in those studies. In contrast, the same proportion of INFASURF-treated neonates compared to beractant-treated neonates in randomized clinical trials (Trials 2) developed intraventricular hemorrhage and periventricular leukomalacia [ see Adverse Reactions (6.2)]. While there is no specific treatment for these complications, affected infants may be at increased risk for neurologic complications, including seizures and neurodevelopmental impairment, and should be monitored as per local guidelines.

6 ADVERSE REACTIONS

The following clinically significant adverse reactions are described elsewhere in the labeling:

- Acute Changes in Oxygenation and Lung Compliance [ see Warnings and Precautions (5.1)]
- Administration-Related Adverse Reactions [see Warnings and Precautions (5.2)]
- Intraventricular Hemorrhage and Periventricular Leukomalacia [ see Warnings and Precautions (5.3)]

6.1 Clinical Trials Experience

Because clinical trials are conducted under widely varying conditions, adverse reaction rates observed in the clinical trials of a drug cannot be directly compared to rates in the clinical trials of another drug and may not reflect the rates observed in practice.

The safety of INFASURF is based on the pooled safety population from three, randomized, active-controlled clinical trials that evaluated INFASURF to reduce the risk of respiratory distress syndrome (RDS) and rescue treatment of RDS [ see Clinical Studies (14)], which included 1,554 preterm neonates who received at least one dose of INFASURF.

The most common INFASURF administration-related adverse reactions were cyanosis (65%), airway obstruction (39%), bradycardia (34%), reflux of surfactant into the endotracheal tube (21%), requirement for manual ventilation (16%), and reintubation (3%).

6.2 Complications of RDS and Neurodevelopmental Outcomes

Incidence of Common Complications of Prematurity

The controlled trials of INFASURF included the incidence of common complications of prematurity and RDS as safety endpoints. Tables 1 and 2 display the results in the INFASURF vs. colfosceril palmitate trials and the INFASURF and beractant trials, respectively. Trials 1, 2, and 3 were not designed to evaluate meaningful comparisons of the incidence of adverse reactions in the INFASURF and the colfosceril palmitate and beractant treatment groups.

Table 1 Common Complications of Prematurity and RDS in Controlled Trials of INFASURF vs colfosceril palmitate
Complication | INFASURF; (N=1,001); % | colfosceril palmitate (N=978); %
Apnea | 61 | 61
Patent ductus arteriosus | 47 | 48
Intracranial hemorrhage | 29 | 31
Severe intracranial hemorrhagea | 12 | 10
IVH and PLVb | 7 | 3
Sepsis | 20 | 22
Pulmonary air leaks | 12 | 22
Pulmonary interstitial emphysema | 7 | 17
Pulmonary hemorrhage | 7 | 7
Necrotizing enterocolitis | 5 | 5
aGrade III and IV by the method of Papile.; bPatients with both intraventricular hemorrhage and periventricular leukomalacia.

Table 2 Common Complications of Prematurity and RDS Controlled Trials of INFASURF vs beractant
Complication | INFASURF; (N=553); % | beractant; (N=566); %
Apnea | 76 | 76
Patent ductus arteriosus | 45 | 48
Intracranial hemorrhage | 36 | 36
Severe intracranial hemorrhagea | 9 | 7
IVH and PVLb | 5 | 5
Sepsis | 28 | 27
Pulmonary air leaks | 15 | 15
Pulmonary interstitial emphysema | 10 | 10
Pulmonary hemorrhage | 7 | 6
Necrotizing enterocolitis | 17 | 18
aGrade III and IV by the method of Papile.
bPatients with both intraventricular hemorrhage and periventricular leukomalacia.

Neurodevelopmental Outcomes

Two-year follow-up data of neurodevelopmental outcomes in 415 neonates who enrolled in the INFASURF vs. colfosceril palmitate controlled-trials demonstrated significant developmental delays in both the INFASURF and colfosceril palmitate groups; however, there was no significant differences between the groups.

8 USE IN SPECIFIC POPULATIONS

8.4 Pediatric Use

The safety and effectiveness of INFASURF have been established to reduce the risk of RDS in preterm neonates < 29 weeks of gestational age at risk for RDS and for the rescue treatment of RDS in preterm neonates ≤72 hours of age with RDS who require endotracheal intubation, and the information on these uses is discussed throughout the labeling. The safety and effectiveness of INFASURF have not been established in older pediatric patients.

10 OVERDOSAGE

If respiration, ventilation, or oxygenation is clearly affected after an accidental overdose, aspirate as much of the intratracheal suspension as possible and provide the neonate with supportive treatment.

11 DESCRIPTION

Calfactant is an extract of natural bovine lung (pulmonary) surfactant consisting of 85% phospholipids, 8% neutral lipids, and 7% hydrophobic surfactant-associated proteins B and C (SP-B and SP-C). The molecular weight of SP-B is 8.7 kDa and the molecular weight of SP-C is 3.7 kDa.

INFASURF (calfactant) intratracheal suspension is a sterile, off-white suspension for intratracheal use. INFASURF contains calfactant at a concentration of 35 mg/mL in either a 105 mg/3 mL or 210 mg/6 mL single-dose vial. Each milliliter of INFASURF contains 35 mg of phospholipids and 0.7 mg of surface-associated proteins of which 0.26 mg is SP-B, a 79-amino acid protein, and 0.44 mg is SP-C, a 35-amino acid peptide. The amount of phospholipids is calculated from the content of phosphorous and contains 26 mg of phosphatidylcholine of which 16 mg is disaturated phosphatidylcholine. It is suspended in 0.9% Sodium Chloride Irrigation, USP. The pH is approximately 5.0 - 6.2 (target pH 5.7).

INFASURF contains no preservatives.

12 CLINICAL PHARMACOLOGY

12.1 Mechanism of Action

Endogenous lung surfactant is essential for effective ventilation because it modifies alveolar surface tension thereby stabilizing the alveoli. Lung surfactant deficiency is the cause of Respiratory Distress Syndrome (RDS) in preterm neonates. INFASURF is a lung surfactant that restores lung surface activity in preterm neonates with RDS by adsorbing to the surface of the air:liquid interface and modifying surface tension similarly to natural lung surfactant.

12.2 Pharmacodynamics

Calfactant dose-response relationships and the time course of pharmacodynamic response are unknown. In vitro, INFASURF lowered minimum surface tension to ≤ 3 mN/m as measured on a pulsating bubble surfactometer. Ex vivo, INFASURF restored the pressure volume mechanics and compliance of surfactant-deficient rat lungs. In vivo, INFASURF improved lung compliance, respiratory gas exchange, and survival in preterm lambs with profound surfactant deficiency.

12.3 Pharmacokinetics

The absorption, distribution, metabolism, and excretion of calfactant in humans following intratracheal administration of INFASURF is unknown.

12.6 Immunogenicity

The immunogenicity of INFASURF is unknown.

13 NONCLINICAL TOXICOLOGY

13.1 Carcinogenesis, Mutagenesis, Impairment of Fertility

Studies to assess potential carcinogenic effects of calfactant have not been conducted.

Calfactant was not mutagenic in a single bacterial reverse mutation assay (Ames test).

No studies to assess reproductive effects of calfactant have been performed.

14 CLINICAL STUDIES

14.1 Overview of Clinical Trials

The efficacy of INFASURF to reduce the risk of respiratory distress syndrome (RDS) in preterm neonates <29 weeks of gestational age at risk for RDS and for the rescue treatment of RDS in preterm neonates ≤72 hours of age with RDS who required endotracheal intubation was based on three randomized, active-controlled clinical trials that enrolled 3,098 neonates:

- INFASURF vs colfosceril palmitate to reduce the risk of RDS in preterm neonates (Trial 1)
- INFASURF vs beractant to reduce the risk of RDS and treatment of RDS in preterm neonates (Trial 2)
- INFASURF vs colfosceril palmitate for treatment of RDS in preterm neonates (Trial 3)

INFASURF vs beractant trial (Trial 2) was one trial that included two cohorts that assessed the efficacy of INFASURF to reduce the risk of RDS (cohort #1) and for the rescue treatment of RDS (cohort #2).

While efficacy cannot be established from uncontrolled trials, there were four uncontrolled trials that included 15,500 preterm neonates who were treated with INFASURF. However, efficacy results are presented only for the three controlled trials described below.

14.2 Reduction of Risk for Neonatal Respiratory Distress Syndrome

INFASURF vs Colfosceril Palmitate Trial to Reduce the Risk of Respiratory Distress Syndrome

A total of 853 neonates <29 weeks gestation were enrolled in a randomized, double-blind, active-controlled, parallel group trial (Trial 1) that compared INFASURF (3 mL/kg) to colfosceril palmitate (5 mL/kg). The initial dose was administered within 30 minutes of birth. If the patient remained intubated, repeat doses were administered every 12 hours (for up to a total of 3 doses). Each dose was divided in 2 equal aliquots and administered intratracheally in small bursts over 20 to 30 inspiratory cycles through a side port adapter into the proximal end of the endotracheal tube. After each aliquot was instilled, the neonate was positioned with either the right or the left side dependent.

The primary efficacy endpoints for this trial were incidence of RDS, incidence of bronchopulmonary dysplasia (BPD) at day 28, and death due to RDS evaluated at 14 days for all treated patients. Select secondary endpoints included death at 28 days or prior to discharge, incidence of air leaks due to RDS, and the cross over to other surfactant treatment. Table 3 displays the efficacy results in this trial.

Table 3 Efficacy Results in Preterm Neonates (< 29 weeks of gestational age) (Trial 1)
 | INFASURF; (N=431); % | colfosceril; palmitate; (N=422); % | p-Value
Primary Endpoints
Incidence of RDS | 15 | 47 | ≤0.001
Bronchopulmonary dysplasiaa | 16 | 17 | 0.60
Death due to RDS | 2 | 5 | ≤0.01
Secondary Endpoints
Any death to 28 days | 12 | 16 | 0.10
Any death before discharge | 18 | 19 | 0.56
Incidence of air leaksb | 10 | 15 | 0.01
Crossover to other surfactantc | 0.2 | 3 | <0.001
aBronchopulmonary dysplasia, diagnosed by positive X-ray and oxygen dependence at 28 days.
bPneumothorax and/or pulmonary interstitial emphysema.
cIf the neonate failed to respond to the three doses of the initial randomized surfactant, was <72 hours of age, and had an a/A PO2ratio <0.1, the neonate was permitted to receive the comparator surfactant.

INFASURF vs. Beractant Trial to Reduce the Risk of Respiratory Distress Syndrome

A total of 1,119 neonates were enrolled in the INFASURF vs beractant trial (Trial 2) which included two cohorts that evaluated INFASURF to reduce the risk of RDS (cohort #1) and for the rescue treatment of RDS (cohort #2) [ see Clinical Studies (14.3)]. Cohort #1 was a randomized, double-blind, active-controlled, trial in 457 neonates ≤ 30 weeks gestation and ≤ 1,250 grams birth weight that compared the 4 mL/kg (100 mg phospholipids/kg) dose of INFASURF to the 4 mL/kg dose of beractant. Note that the INFASURF formulation and dose used in this trial were different from the marketed INFASURF formulation and the recommended dose of 3 mL/kg (105 mg phospholipid/kg). The initial dose was administered intratracheally within 15 minutes of birth and if the patient required ≥30% oxygen repeat doses were administered intratracheally at ≥6 hours following the previous INFASURF dose (for a total of 3 repeat doses before 96 hours of age (a total of 4 doses including the initial dose and the repeat doses)); the recommended frequency of INFASURF repeat dosing is every 12 hours and the maximum number of doses including the initial and repeat doses is three [ see Dosage and Administration (2.1)]. The surfactant treatments were administered through a 5-French feeding catheter inserted into the endotracheal tube. Each dose was instilled in four equal aliquots (between each of the instillations, the catheter was removed and mechanical ventilation resumed for 0.5 to 2 minutes). Each of the aliquots was administered with the patient in one of four different positions (prone, supine, right, and left lateral).

There was increased mortality from any cause at 28 days (p=0.03) and in death due to respiratory causes (p=0.005) in INFASURF-treated neonates compared to beractant-treated neonates. For evaluable patients (patients who met the protocol-defined entry criteria), mortality from any cause and mortality due to respiratory causes were also higher in the INFASURF group (p = 0.07 and 0.03, respectively). However, these observations have not been replicated in other adequate and well-controlled trials and their relevance to the intended population is unknown. There was no significant difference in the incidence of RDS, air leaks, BPD, and treatment failure between INFASURF and beractant groups.

14.3 Rescue Treatment of Neonatal Respiratory Distress Syndrome

INFASURF vs Colfosceril Palmitate Trial for the Rescue Treatment of Respiratory Distress Syndrome

A total of 1,126 neonates ≤72 hours of age with RDS who required endotracheal intubation and had an arterial/Alveolar oxygen ratio (a/A) PO2< 0.22 were enrolled into a randomized, double-blind, active-control, parallel group trial (Trial 3) that compared INFASURF (3 mL/kg) and colfosceril palmitate (5 mL/kg). Patients received an initial dose, and if intubation was still required, patients received one repeat dose 12 hours later (total of 2 doses). Each dose was instilled intratracheally in small bursts over 20 to 30 inspiratory cycles in two aliquots through a side-port adapter into the proximal end of the endotracheal tube. After each aliquot was instilled, the neonate was positioned with either the right or the left side dependent.

The primary efficacy endpoints for this trial were the incidence of RDS-related air leaks, incidence of BPD at 28 days, and mortality secondary to RDS. Select secondary endpoints included any death at day 28 or prior to hospital discharge and crossover to other surfactant. Table 4 describes the efficacy results of this trial.

Table 4 Efficacy Results in Neonates ≤72 Hours of Age (Trial 3)
 | INFASURF (N=570) % | colfosceril; palmitate; (N=556); % | p-Value
Primary Endpoints
Air leaksa | 11 | 22 | ≤0.001
BPDb | 5 | 6 | 0.41
Death due to RDS | 4 | 4 | 0.95
Secondary Endpoints
Any death to 28 days | 8 | 10 | 0.21
Any death before discharge | 9 | 12 | 0.07
Crossover to other surfactantc | 4 | 4 | 1
aPneumothorax and/or pulmonary interstitial emphysema.
bBPD is bronchopulmonary dysplasia, diagnosed by positive X-ray and oxygen dependence at 28 days.
cIf the neonate failed to respond to the two doses of the initial randomized surfactant, was <96 hours of age, and had an a/A PO2ratio <0.1, the neonate was permitted to receive the comparator surfactant.

INFASURF versus Beractant Trial for the Rescue Treatment of Respiratory Distress Syndrome

A total of 1,119 neonates were enrolled in the INFASURF vs. beractant trial (Trial 2) which included two cohorts that evaluated INFASURF to reduce risk of RDS (cohort #1) [ see Clinical Studies (14.2)] and for rescue treatment of RDS (cohort #2). Cohort #2 was a randomized, double-blind, active-controlled trial in 662 neonates with RDS who required endotracheal intubation and had an a/A PO2<0.22 that compared the 4 mL/kg (100 mg phospholipids/kg) dose of INFASURF to the 4 mL/kg dose of beractant. Note that the INFASURF formulation and dose used in this trial were different from the marketed INFASURF formulation and the recommended dose of 3 mL/kg (105 mg phospholipids/kg). If the neonate required ≥30% oxygen, repeat doses were administered at ≥6 hours following the previous treatment (for a total of four doses before 96 hours of age). Note that the recommended frequency of INFASURF repeat dosing is every 12 hours and the maximum number of doses including the initial and repeat doses is three [ see Dosage and Administration (2.1)]. The surfactant was administered intratracheally through a 5-French feeding catheter inserted into the endotracheal tube. Each dose was instilled in four equal aliquots (the catheter was removed between each of the instillations and mechanical ventilation resumed for 0.5 to 2 minutes). Each of the aliquots was administered with the patient in one of four different positions (prone, supine, right, and left lateral) to facilitate even distribution of the surfactant.

The primary efficacy endpoints were the incidence of air leaks, death due to respiratory causes or to any cause, BPD, or treatment failure evaluated at 28 days or to discharge. There was no significant difference between the INFASURF and beractant groups in these efficacy endpoints.

16 HOW SUPPLIED/STORAGE AND HANDLING

INFASURF (calfactant) intratracheal suspension is an off-white suspension available in a sterile, rubber-stoppered glass single-dose vial packaged as one vial per carton:

- 105 mg/3 mL (35 mg/mL) (NDC 61938-456-03)
- 210 mg/6 mL (35 mg/mL) (NDC 61938-456-06)

Refrigerate INFASURF (calfactant) intratracheal suspension at 2°C to 8°C (36°F to 46°F) and protect from light. Must store the 105 mg/3 mL (35 mg/mL) vial upright. Do not remove INFASURF from the refrigerator for more than 24 hours.

Unopened, unused INFASURF vials that have reached room temperature within 24 hours can be refrigerated for future use; however, do not re-refrigerate INFASURF more than once. Record the date and time on the carton when INFASURF is removed from the refrigerator.

17 PATIENT COUNSELING INFORMATION

Inform caregivers of the following risks of INFASURF:

- Advise patient’s caregivers of acute changes in oxygenation and/or lung function typically occur when a surfactant-deficient neonate with respiratory distress is given a surfactant, including INFASURF [ see Warnings and Precautions, (5.1)].

- Advise patient’s caregivers of temporary adverse reactions, including skin turning blue, heart rate slowing, airway blockage, or reflux of INFASURF into the infant’s breathing tube may occur when INFASURF is administered [ see Warnings and Precautions (5.2)]. If any of these adverse reactions occurs, the healthcare provider will interrupt INFASURF administration and take appropriate measures to alleviate the adverse reactions.

- Advise patient’s caregivers that infants treated with INFASURF may have evidence of bleeding into the brain and/or loss of brain tissue [ see Warning and Precautions (5.3)]. Bleeding into the brain and loss of brain tissue are sometimes seen in preterm infants, including those who do not receive surfactant treatment, since the main risk factor is being born at or before 32 weeks’ gestation. There is no treatment for these complications but affected infants may be at risk for later neurologic complications, including seizures and/or developmental delay, and may require additional evaluation after discharge from the hospital.

Manufactured by:

ONY Biotech Inc.

455 Commerce Drive

Amherst, NY 14228

U.S. License No. 2192